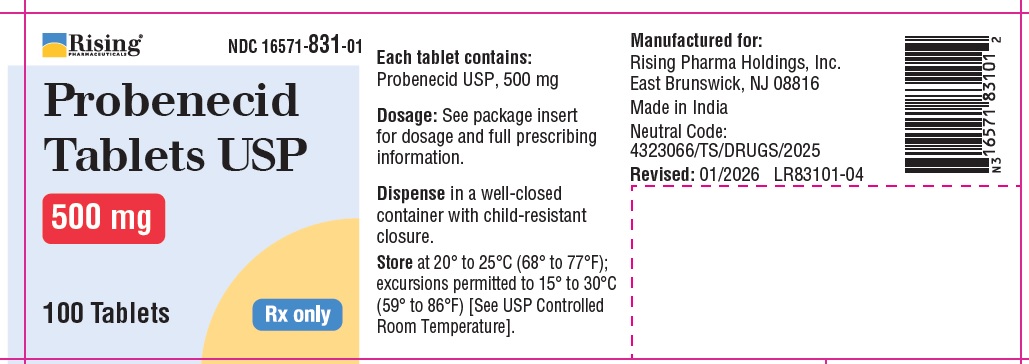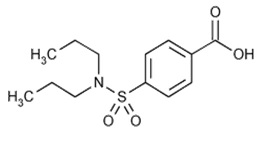 DRUG LABEL: Probenecid
NDC: 16571-831 | Form: TABLET
Manufacturer: Rising Pharma Holdings, Inc.
Category: prescription | Type: Human Prescription Drug Label
Date: 20260128

ACTIVE INGREDIENTS: PROBENECID 500 mg/1 1
INACTIVE INGREDIENTS: SILICON DIOXIDE; STARCH, CORN; D&C YELLOW NO. 10; FD&C BLUE NO. 2; FD&C RED NO. 40; MAGNESIUM STEARATE; MICROCRYSTALLINE CELLULOSE 101; POLYETHYLENE GLYCOL 4000; POLYVINYL ALCOHOL; POVIDONE K90; SODIUM LAURYL SULFATE; SODIUM STARCH GLYCOLATE TYPE A POTATO; TALC; TITANIUM DIOXIDE

Probenecid Tablets USP, 500 mg
Rx only

DESCRIPTION

Probenecid is a uricosuric and renal tubular transport blocking agent.
Probenecid is the generic name for 4-[(dipropyl-amino)sulfonyl] benzoic acid. It has the following structural formula:

C13H19NO4S M.W. 285.36
Probenecid USP is a white or practically white, fine, crystalline powder. Probenecid is soluble in dilute alkali, in alcohol, in chloroform, and in acetone; it is practically insoluble in water and in dilute acids.
Each tablet for oral administration contains 500 mg of probenecid.
Probenecid Tablets USP 500 mg contain the following inactive ingredients: colloidal silicon dioxide, corn starch, D&C Yellow No. 10, FD&C Blue No. 2, FD&C Red No. 40, magnesium stearate, microcrystalline cellulose, polyethylene glycol, polyvinyl alcohol, povidone, sodium lauryl sulphate, sodium starch glycolate, talc and titanium dioxide.
FDA approved dissolution test specifications differ from USP.

CLINICAL PHARMACOLOGY

Probenecid is a uricosuric and renal tubular blocking agent. It inhibits the tubular reabsorption of urate, thus increasing the urinary excretion of uric acid and decreasing serum urate levels. Effective uricosuria reduces the miscible urate pool, retards urate deposition, and promotes resorption of urate deposits.
Probenecid inhibits the tubular secretion of penicillin and usually increases penicillin plasma levels by any route the antibiotic is given. A 2-fold to 4-fold elevation has been demonstrated for various penicillins.
Probenecid has also been reported to inhibit the renal transport of many other compounds including aminohippuric acid (PAH), aminosalicylic acid (PAS), indomethacin, sodium iodomethamate and related iodinated organic acids, 17-ketosteroids, pantothenic acid, phenolsulfonphthalein (PSP), sulfonamides, and sulfonylureas. See also Drug Interactions.
Probenecid decreases both hepatic and renal excretion of sulfobromophthalein (BSP). The tubular reabsorption of phosphorus is inhibited in hypoparathyroid but not in euparathyroid individuals.
Probenecid does not influence plasma concentrations of salicylates, nor the excretion of streptomycin, chloramphenicol, chlortetracycline, oxytetracycline, or neomycin.

INDICATIONS & USAGE

Probenecid tablets are indicated for the treatment of the hyperuricemia associated with gout and gouty arthritis.
As an adjuvant to therapy with penicillin or with ampicillin, methicillin, oxacillin, cloxacillin, or nafcillin, for elevation and prolongation of plasma levels by whatever route the antibiotic is given.

CONTRAINDICATIONS

Hypersensitivity to probenecid.
Children under 2 years of age.
Not recommended in persons with known blood dyscrasias or uric acid kidney stones.
Therapy with probenecid should not be started until an acute gouty attack has subsided.

WARNINGS

Exacerbation of gout following therapy with probenecid may occur; in such cases colchicine or other appropriate therapy is advisable.
Probenecid increases plasma concentrations of methotrexate in both animals and humans. In animal studies, increased methotrexate toxicity has been reported. If probenecid is given with methotrexate, the dosage of methotrexate should be reduced and serum levels may need to be monitored.
In patients on probenecid the use of salicylates in either small or large doses is contraindicated because it antagonizes the uricosuric action of probenecid. The biphasic action of salicylates in the renal tubules accounts for the so-called “paradoxical effect” of uricosuric agents. In patients on probenecid who require a mild analgesic agent the use of acetaminophen rather than small doses of salicylates would be preferred.
Rarely, severe allergic reactions and anaphylaxis have been reported with the use of probenecid. Most of these have been reported to occur within several hours after readministration following prior usage of the drug.
The appearance of hypersensitivity reactions requires cessation of therapy with probenecid.
Use in Pregnancy
Probenecid crosses the placental barrier and appears in cord blood. The use of any drug in women of childbearing potential requires that the anticipated benefit be weighed against possible hazards.

PRECAUTIONS

General

Hematuria, renal colic, costovertebral pain, and formation of uric acid stones associated with the use of probenecid in gouty patients may be prevented by alkalization of the urine and a liberal fluid intake (see DOSAGE AND ADMINISTRATION). In these cases when alkali is administered, the acid-base balance of the patient should be watched.
Use with caution in patients with a history of peptic ulcer.
Probenecid has been used in patients with some renal impairment but dosage requirements may be increased. Probenecid may not be effective in chronic renal insufficiency particularly when the glomerular filtration rate is 30 mL/minute or less. Because of its mechanism of action, probenecid is not recommended in conjunction with a penicillin in the presence of known renal impairment.
A reducing substance may appear in the urine of patients receiving probenecid. This disappears with discontinuance of therapy. Suspected glycosuria should be confirmed by using a test specific for glucose.

Drug Interactions

When probenecid is used to elevate plasma concentrations of penicillin or other beta-lactams, or when such drugs are given to patients taking probenecid therapeutically, high plasma concentrations of the other drug may increase the incidence of adverse reactions associated with that drug. In the case of penicillin or other beta-lactams, psychic disturbances have been reported.
The use of salicylates antagonizes the uricosuric action of probenecid (see WARNINGS). The uricosuric action of probenecid is also antagonized by pyrazinamide.
Probenecid produces an insignificant increase in free sulfonamide plasma concentrations but a significant increase in total sulfonamide plasma levels. Since probenecid decreases the renal excretion of conjugated sulfonamides, plasma concentrations of the latter should be determined from time to time when a sulfonamide and probenecid are coadministered for prolonged periods. Probenecid may prolong or enhance the action of oral sulfonylureas and thereby increase the risk of hypoglycemia.
It has been reported that patients receiving probenecid require significantly less thiopental for induction of anesthesia. In addition, ketamine and thiopental anesthesia were significantly prolonged in rats receiving probenecid.
The concomitant administration of probenecid increases the mean plasma elimination half-life of a number of drugs which can lead to increased plasma concentrations. These include agents such as indomethacin, acetaminophen, naproxen, ketoprofen, meclofenamate, lorazepam, and rifampin. Although the clinical significance of this observation has not been established, a lower dosage of the drug may be required to produce a therapeutic effect, and increases in dosage of the drug in question should be made cautiously and in small increments when probenecid is being co-administered. Although specific instances of toxicity due to this potential interaction have not been observed to date, physicians should be alert to this possibility.
Probenecid given concomitantly with sulindac had only a slight effect on plasma sulfide levels, while plasma levels of sulindac and sulfone were increased. Sulindac was shown to produce a modest reduction in the uricosuric action of probenecid, which probably is not significant under most circumstances.
In animals and in humans, probenecid has been reported to increase plasma concentrations of methotrexate (see WARNINGS).
Falsely high readings for theophylline have been reported in an in vitro study, using the Schack and Waxler technique, when therapeutic concentrations of theophylline and probenecid were added to human plasma.

ADVERSE REACTIONS

The following adverse reactions have been observed and within each category are listed in order of decreasing severity.
Central Nervous System: headache, dizziness.
Metabolic: precipitation of acute gouty arthritis.
Gastrointestinal: hepatic necrosis, vomiting, nausea, anorexia, sore gums.
Genitourinary: nephrotic syndrome, uric acid stones with or without hematuria, renal colic,
costovertebral pain, urinary frequency.
Hypersensitivity: anaphylaxis, fever, urticaria, pruritus.
Hematologic: aplastic anemia, leukopenia, hemolytic anemia which in some patients could be related to genetic deficiency of glucose-6-phosphate dehydrogenase in red blood cells, anemia.
Integumentary: dermatitis, alopecia, flushing.
To report SUSPECTED ADVERSE REACTIONS, contact Rising Pharma Holdings, Inc. at 1-844-874-7464 or FDA at 1-800-FDA-1088 or www.fda.gov/medwatch.

DOSAGE & ADMINISTRATION

Gout
Therapy with probenecid should not be started until an acute gouty attack has subsided. However, if an acute attack is precipitated during therapy, probenecid may be continued without changing the dosage, and full therapeutic dosage of colchicine or other appropriate therapy should be given to control the acute attack.
The recommended adult dosage is 250 mg (1/2 tablet of probenecid) twice a day for one week, followed by 500 mg (1 tablet) twice a day thereafter.
Some degree of renal impairment may be present in patients with gout. A daily dosage of 1000 mg may be adequate. However, if necessary, the daily dosage may be increased by 500 mg increments every 4 weeks within tolerance (and usually not above 2000 mg per day) if symptoms of gouty arthritis are not controlled or the 24 hour uric acid excretion is not above 700 mg. As noted, probenecid may not be effective in chronic renal insufficiency, particularly when the glomerular filtration rate is 30 mL/minute or less.
Gastric intolerance may be indicative of overdosage, and may be corrected by decreasing the dosage.
As uric acid tends to crystallize out of an acid urine, a liberal fluid intake is recommended, as well as sufficient sodium bicarbonate (3 to 7.5 g daily), or potassium citrate (7.5 g daily) to maintain an alkaline urine (see PRECAUTIONS).
Alkalization of the urine is recommended until the serum urate level returns to normal limits and tophaceous deposits disappear, i.e., during the period when urinary excretion of uric acid is at a high level. Thereafter, alkalization of the urine and the usual restriction of purine-producing foods may be somewhat relaxed.
Probenecid should be continued at the dosage that will maintain normal serum urate levels. When acute attacks have been absent for 6 months or more and serum urate levels remain within normal limits, the daily dosage may be decreased by 500 mg every 6 months. The maintenance dosage should not be reduced to the point where serum urate levels tend to rise.
Probenecid and Penicillin Therapy (General)
Adults
The recommended dosage is 2000 mg (4 tablets of probenecid) daily in divided doses. This dosage should be reduced in older patients in whom renal impairment may be present.
Children 2 to 14 years of age
Initial dose: 25 mg/kg body weight (or 0.7 g/square meter body surface).
Maintenance dose: 40 mg/kg body weight (or 1.2 g/square meter body surface) per day, divided into 4 doses.
For children weighing more than 50 kg (110 lb) the adult dosage is recommended.
Probenecid is contraindicated in children under 2 years of age.
The PSP excretion test may be used to determine the effectiveness of probenecid in retarding penicillin excretion and maintaining therapeutic levels. The renal clearance of PSP is reduced to about one-fifth the normal rate when dosage of probenecid is adequate.
Penicillin Therapy (Gonorrhea)*

In uncomplicated gonococcal infections in men and women (urethral, cervical, rectal), 1 g of probenecid should be given orally with 4.8 million units of aqueous procaine penicillin G** (given IM), or 3 g of amoxicillin** (given orally), or 3.5 g of ampicillin** (given orally).

For further guidance, see CDC recommendations for definition of regimens of choice, alternative regimens, treatment of hypersensitive patients, and other aspects of therapy.
*Recommended by the Centers for Disease Control, U.S. Department of Health and Human Services, Public Health Service (Morbidity and Mortality Weekly Report Supplement, Volume 34, Number 4S, October 18, 1985).
**See package circulars of manufacturers for detailed information about CONTRAlNDICATIONS, WARNINGS, PRECAUTIONS, and ADVERSE REACTIONS.

HOW SUPPLIED

Probenecid Tablets USP, 500 mg are bisected, capsule-shaped, yellow, film-coated tablets debossed with “C84” on one side and break line on other side.
They are supplied in bottles as follows:
100 count: NDC 16571-831-01
1,000 count: NDC 16571-831-10
Dispense in well-closed container with child-resistant closure.
Store at 20° to 25°C (68° to 77°F); excursions permitted to 15° to 30°C (59° to 86°F) [See USP Controlled Room Temperature].
Manufactured for:
Rising Pharma Holdings, Inc.
East Brunswick, NJ 08816
Made in India.
Neutral Code: 4323066/TS/DRUGS/2025
Revised: 01/2026
PIR83110-05

PACKAGE LABEL.PRINCIPAL DISPLAY PANEL

NDC 16571-831-01
Probenecid Tablets USP
500 mg
100 Tablets
Rising Pharma Holdings, Inc.
Rx only